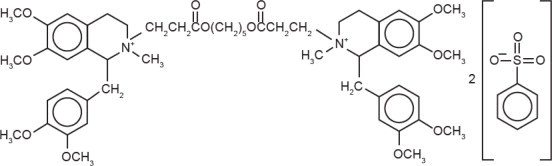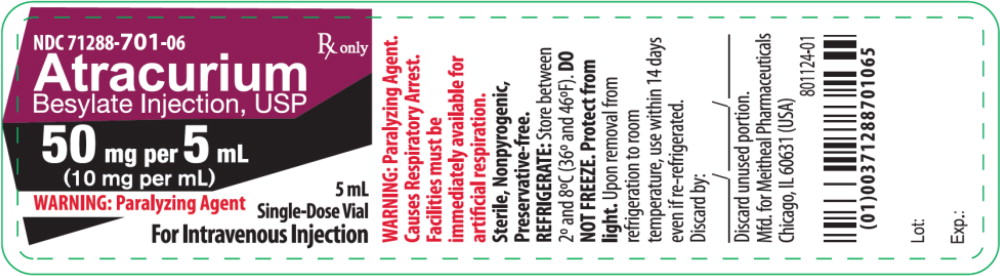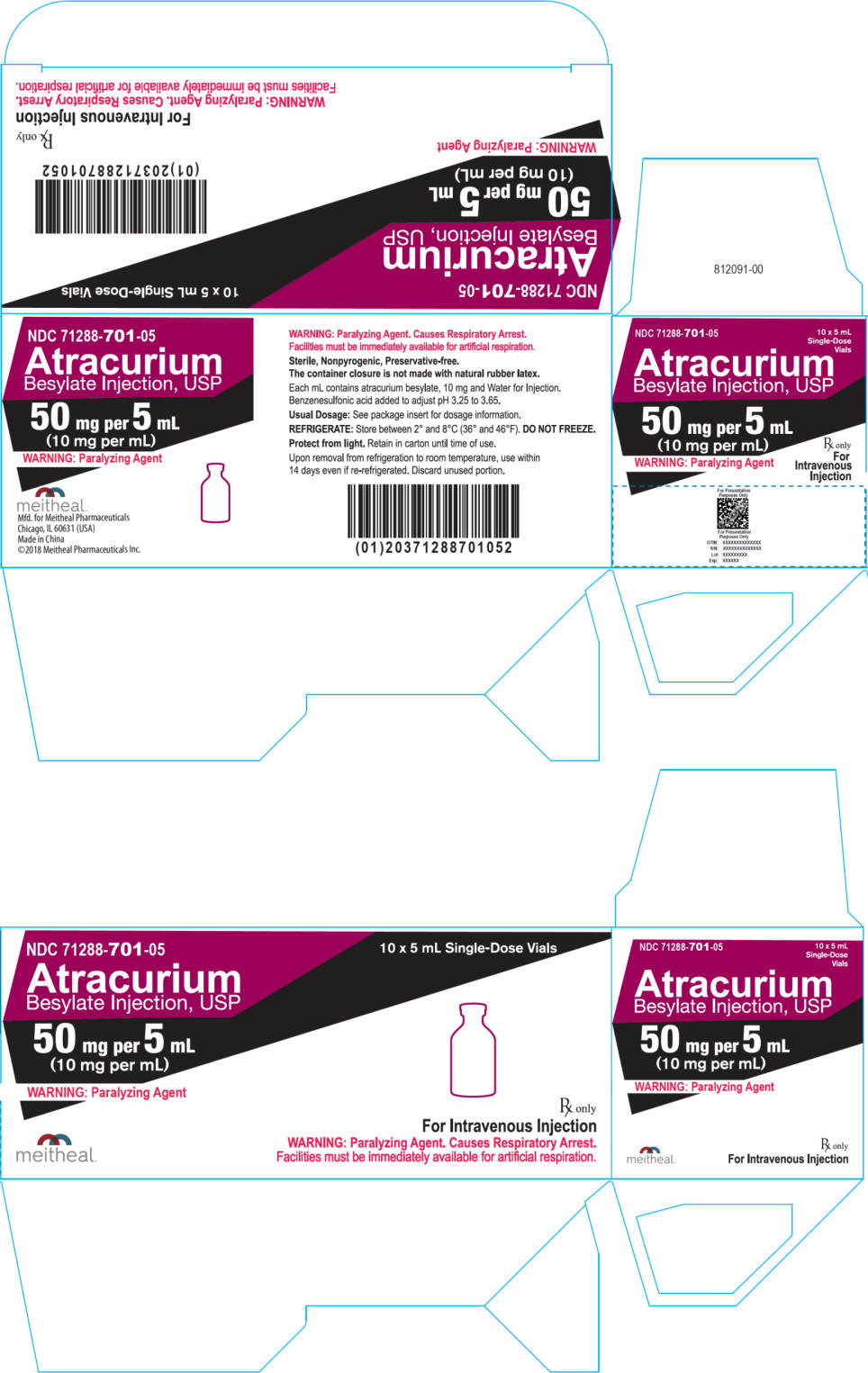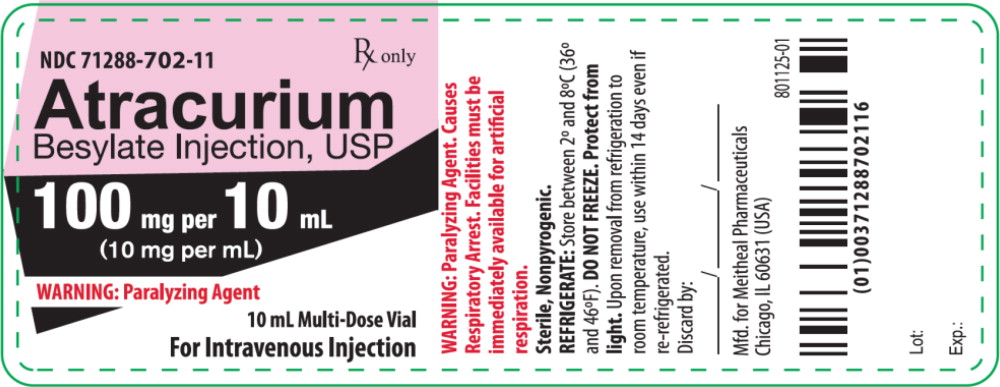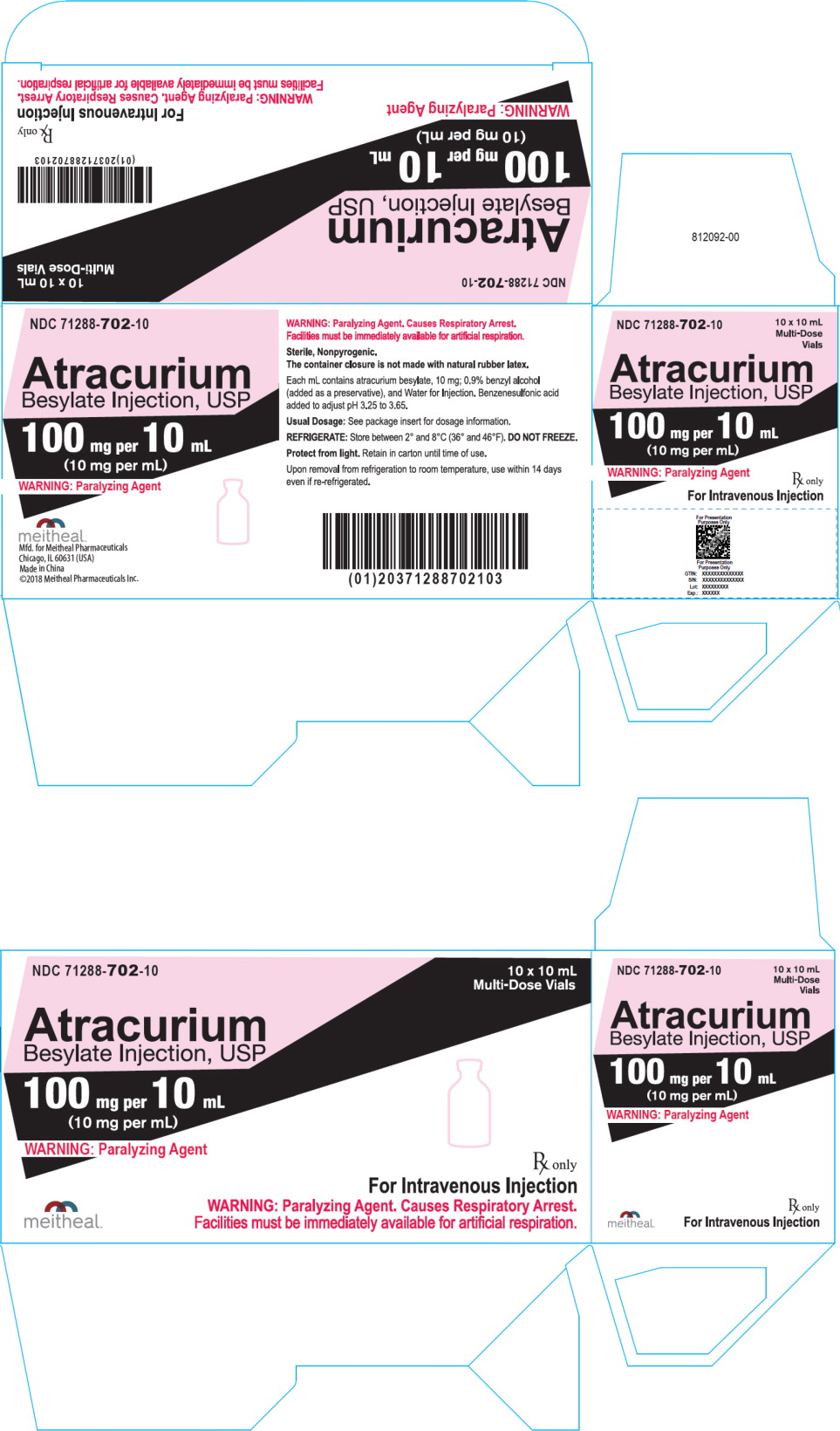 DRUG LABEL: Atracurium Besylate
NDC: 71288-701 | Form: INJECTION, SOLUTION
Manufacturer: Meitheal Pharmaceuticals Inc.
Category: prescription | Type: HUMAN PRESCRIPTION DRUG LABEL
Date: 20241204

ACTIVE INGREDIENTS: Atracurium Besylate 10 mg/1 mL
INACTIVE INGREDIENTS: benzenesulfonic acid; water

Atracurium Besylate Injection, USP
(For Intravenous Injection)

meitheal®
Rx only

This drug should be used only by adequately trained individuals familiar with its actions, characteristics, and hazards.

DESCRIPTION

Atracurium besylate is an intermediate-duration, nondepolarizing, skeletal muscle relaxant for intravenous administration. Atracurium besylate is designated as 2-(2-Carboxyethyl)-1,2,3,4-tetrahydro-6,7-dimethoxy-2-methyl-1-veratrylisoquinolinium benzenesulfonate, pentamethylene ester. It has a molecular weight of 1243.49, and its molecular formula is C65H82N2O18S2. The structural formula is:

Atracurium besylate is a complex molecule containing four sites at which different stereochemical configurations can occur. The symmetry of the molecule, however, results in only ten, instead of sixteen, possible different isomers. The manufacture of atracurium besylate results in these isomers being produced in unequal amounts but with a consistent ratio. Those molecules in which the methyl group attached to the quaternary nitrogen projects on the opposite side to the adjacent substituted-benzyl moiety predominate by approximately 3:1.

Atracurium Besylate Injection, USP is a sterile, non-pyrogenic aqueous solution. Each mL contains 10 mg atracurium besylate. The pH is adjusted to 3.25 to 3.65 with benzenesulfonic acid. The multiple dose vial contains 0.9% benzyl alcohol added as a preservative. Atracurium besylate injection slowly loses potency with time at the rate of approximately 6% per year under refrigeration (5°C). Atracurium besylate injection should be refrigerated at 2° to 8°C (36° to 46°F) to preserve potency. Rate of loss in potency increases to approximately 5% per month at 25°C (77°F). Upon removal from refrigeration to room temperature storage conditions (25°C / 77°F), use atracurium besylate injection within 14 days even if re-refrigerated.

CLINICAL PHARMACOLOGY

Atracurium besylate is a nondepolarizing skeletal muscle relaxant. Nondepolarizing agents antagonize the neurotransmitter action of acetylcholine by binding competitively with cholinergic receptor sites on the motor end-plate. This antagonism is inhibited, and neuromuscular block reversed, by acetylcholinesterase inhibitors such as neostigmine, edrophonium, and pyridostigmine.

Atracurium can be used most advantageously if muscle twitch response to peripheral nerve stimulation is monitored to assess degree of muscle relaxation.

The duration of neuromuscular block produced by atracurium is approximately one-third to one-half the duration of block by d-tubocurarine, metocurine, and pancuronium at initially equipotent doses. As with other nondepolarizing neuromuscular blockers, the time to onset of paralysis decreases and the duration of maximum effect increases with increasing atracurium doses.

The ED95 (dose required to produce 95% suppression of the muscle twitch response with balanced anesthesia) has averaged 0.23 mg/kg (0.11 to 0.26 mg/kg in various studies). An initial atracurium dose of 0.4 to 0.5 mg/kg generally produces maximum neuromuscular block within 3 to 5 minutes of injection, with good or excellent intubation conditions within 2 to 2.5 minutes in most patients. Recovery from neuromuscular block (under balanced anesthesia) can be expected to begin approximately 20 to 35 minutes after injection. Under balanced anesthesia, recovery to 25% of control is achieved approximately 35 to 45 minutes after injection, and recovery is usually 95% complete approximately 60 to 70 minutes after injection. The neuromuscular blocking action of atracurium is enhanced in the presence of potent inhalation anesthetics. Isoflurane and enflurane increase the potency of atracurium and prolong neuromuscular block by approximately 35%; however, halothane's potentiating effect (approximately 20%) is marginal (see DOSAGE AND ADMINISTRATION).

Repeated administration of maintenance doses of atracurium has no cumulative effect on the duration of neuromuscular block if recovery is allowed to begin prior to repeat dosing. Moreover, the time needed to recover from repeat doses does not change with additional doses. Repeat doses can therefore be administered at relatively regular intervals with predictable results. After an initial dose of 0.4 to 0.5 mg/kg under balanced anesthesia, the first maintenance dose (suggested maintenance dose is 0.08 to 0.10 mg/kg) is generally required within 20 to 45 minutes, and subsequent maintenance doses are usually required at approximately 15 to 25 minute intervals.

Once recovery from atracurium's neuromuscular blocking effects begins, it proceeds more rapidly than recovery from d-tubocurarine, metocurine, and pancuronium. Regardless of the atracurium dose, the time from start of recovery (from complete block) to complete (95%) recovery is approximately 30 minutes under balanced anesthesia, and approximately 40 minutes under halothane, enflurane or isoflurane. Repeated doses have no cumulative effect on recovery rate.

Reversal of neuromuscular block produced by atracurium can be achieved with an anticholinesterase agent such as neostigmine, edrophonium, or pyridostigmine, in conjunction with an anticholinergic agent such as atropine or glycopyrrolate. Under balanced anesthesia, reversal can usually be attempted approximately 20 to 35 minutes after an initial atracurium besylate dose of 0.4 to 0.5 mg/kg, or approximately 10 to 30 minutes after a 0.08 to 0.10 mg/kg maintenance dose, when recovery of muscle twitch has started. Complete reversal is usually attained within 8 to 10 minutes of the administration of reversing agents. Rare instances of breathing difficulties, possibly related to incomplete reversal, have been reported following attempted pharmacologic antagonism of atracurium-induced neuromuscular block. As with other agents in this class, the tendency for residual neuromuscular block is increased if reversal is attempted at deep levels of block or if inadequate doses of reversal agents are employed.

The pharmacokinetics of atracurium in humans are essentially linear within the 0.3 to 0.6 mg/kg dose range. The elimination half-life is approximately 20 minutes. THE DURATION OF NEUROMUSCULAR BLOCK PRODUCED BY ATRACURIUM BESYLATE DOES NOT CORRELATE WITH PLASMA PSEUDOCHOLINESTERASE LEVELS AND IS NOT ALTERED BY THE ABSENCE OF RENAL FUNCTION. This is consistent with the results of in vitro studies which have shown that atracurium is inactivated in plasma via two nonoxidative pathways: ester hydrolysis, catalyzed by nonspecific esterases; and Hofmann elimination, a nonenzymatic chemical process which occurs at physiological pH. Some placental transfer occurs in humans.

Radiolabel studies demonstrated that atracurium undergoes extensive degradation in cats, and that neither kidney nor liver plays a major role in this elimination. Biliary and urinary excretion were the major routes of excretion of radioactivity (totaling >90% of the labeled dose within 7 hours of dosing), of which atracurium represented only a minor fraction. The metabolites in bile and urine were similar, including products of Hofmann elimination and ester hydrolysis.

Elderly patients may have slightly altered pharmacokinetic parameters compared to younger patients, with a slightly decreased total plasma clearance which is offset by a corresponding increase in volume of distribution. The net effect is that there has been no significant difference in clinical duration and recovery from neuromuscular block observed between elderly and younger patients receiving atracurium besylate.

Atracurium is a less potent histamine releaser than d-tubocurarine or metocurine. Histamine release is minimal with initial atracurium besylate doses up to 0.5 mg/kg, and hemodynamic changes are minimal within the recommended dose range. A moderate histamine release and significant falls in blood pressure have been seen following 0.6 mg/kg of atracurium besylate. The histamine and hemodynamic responses were poorly correlated. The effects were generally short-lived and manageable, but the possibility of substantial histamine release in sensitive individuals or in patients in whom substantial histamine release would be especially hazardous (e.g., patients with significant cardiovascular disease) must be considered.

It is not known whether the prior use of other nondepolarizing neuromuscular blocking agents has any effect on the activity of atracurium. The prior use of succinylcholine decreases by approximately 2 to 3 minutes the time to maximum block induced by atracurium besylate, and may increase the depth of block. Atracurium should be administered only after a patient recovers from succinylcholine-induced neuromuscular block.

INDICATIONS AND USAGE

Atracurium besylate injection is indicated, as an adjunct to general anesthesia, to facilitate endotracheal intubation and to provide skeletal muscle relaxation during surgery or mechanical ventilation.

CONTRAINDICATIONS

Atracurium besylate is contraindicated in patients known to have a hypersensitivity to it. Use of atracurium besylate from multiple dose vials containing benzyl alcohol as a preservative is contraindicated in patients with a known hypersensitivity to benzyl alcohol.

WARNINGS

ATRACURIUM SHOULD BE USED ONLY BY THOSE SKILLED IN AIRWAY MANAGEMENT AND RESPIRATORY SUPPORT. EQUIPMENT AND PERSONNEL MUST BE IMMEDIATELY AVAILABLE FOR ENDOTRACHEAL INTUBATION AND SUPPORT OF VENTILATION, INCLUDING ADMINISTRATION OF POSITIVE PRESSURE OXYGEN. ADEQUACY OF RESPIRATION MUST BE ASSURED THROUGH ASSISTED OR CONTROLLED VENTILATION. ANTICHOLINESTERASE REVERSAL AGENTS SHOULD BE IMMEDIATELY AVAILABLE.

DO NOT GIVE ATRACURIUM BESYLATE BY INTRAMUSCULAR ADMINISTRATION.

Atracurium has no known effect on consciousness, pain threshold, or cerebration. It should be used only with adequate anesthesia.

Atracurium besylate injection, which has an acid pH, should not be mixed with alkaline solutions (e.g., barbiturate solutions) in the same syringe or administered simultaneously during intravenous infusion through the same needle. Depending on the resultant pH of such mixtures, atracurium may be inactivated and a free acid may be precipitated.

Atracurium besylate injection 10 mL multiple dose vials contain benzyl alcohol. In neonates, benzyl alcohol has been associated with an increased incidence of neurological and other complications which are sometimes fatal. Atracurium besylate 5 mL single use vials do not contain benzyl alcohol (see PRECAUTIONS, Pediatric Use).

Anaphylaxis

Severe anaphylactic reactions to neuromuscular blocking agents, including atracurium besylate, have been reported. These reactions have in some cases been life-threatening and fatal. Due to the potential severity of these reactions, the necessary precautions, such as the immediate availability of appropriate emergency treatment, should be taken. Precautions should also be taken in those individuals who have had previous anaphylactic reactions to other neuromuscular blocking agents since cross-reactivity between neuromuscular blocking agents, both depolarizing and non-depolarizing, has been reported in this class of drugs.

Risk of Death Due to Medication Errors

Administration of atracurium besylate injection results in paralysis, which may lead to respiratory arrest and death; this progression may be more likely to occur in a patient for whom it is not intended. Confirm proper selection of intended product and avoid confusion with other injectable solutions that are present in critical care and other clinical settings. If another healthcare provider is administering the product, ensure that the intended dose is clearly labeled and communicated.

PRECAUTIONS

Since allergic cross-reactivity has been reported in this class, request information from your patients about previous anaphylactic reactions to other neuromuscular blocking agents. In addition, inform your patients that severe anaphylactic reactions to neuromuscular blocking agents, including atracurium besylate have been reported.

General

Although atracurium is a less potent histamine releaser than d-tubocurarine or metocurine, the possibility of substantial histamine release in sensitive individuals must be considered. Special caution should be exercised in administering atracurium to patients in whom substantial histamine release would be especially hazardous (e.g., patients with clinically significant cardiovascular disease) and in patients with any history (e.g., severe anaphylactoid reactions or asthma) suggesting a greater risk of histamine release. In these patients, the recommended initial atracurium besylate dose is lower (0.3 to 0.4 mg/kg) than for other patients and should be administered slowly or in divided doses over one minute.

Since atracurium has no clinically significant effects on heart rate in the recommended dosage range, it will not counteract the bradycardia produced by many anesthetic agents or vagal stimulation. As a result, bradycardia during anesthesia may be more common with atracurium than with other muscle relaxants.

Atracurium may have profound effects in patients with myasthenia gravis, Eaton-Lambert syndrome, or other neuromuscular diseases in which potentiation of nondepolarizing agents has been noted. The use of a peripheral nerve stimulator is especially important for assessing neuromuscular block in these patients. Similar precautions should be taken in patients with severe electrolyte disorders or carcinomatosis.

Multiple factors in anesthesia practice are suspected of triggering malignant hyperthermia (MH), a potentially fatal hypermetabolic state of skeletal muscle. Halogenated anesthetic agents and succinylcholine are recognized as the principal pharmacologic triggering agents in MH-susceptible patients; however, since MH can develop in the absence of established triggering agents, the clinician should be prepared to recognize and treat MH in any patient scheduled for general anesthesia. Reports of MH have been rare in cases in which atracurium has been used. In studies of MH-susceptible animals (swine) and in a clinical study of MH-susceptible patients, atracurium did not trigger this syndrome.

Resistance to nondepolarizing neuromuscular blocking agents may develop in burn patients. Increased doses of nondepolarizing muscle relaxants may be required in burn patients and are dependent on the time elapsed since the burn injury and the size of the burn.

The safety of atracurium has not been established in patients with bronchial asthma.

Long-Term Use in Intensive Care Unit (ICU)

When there is a need for long-term mechanical ventilation, the benefits-to-risk ratio of neuromuscular block must be considered. The long-term (1 to 10 days) infusion of atracurium besylate during mechanical ventilation in the ICU has been evaluated in several studies. Average infusion rates of 11 to 13 mcg/kg per minute (range: 4.5 to 29.5) were required to achieve adequate neuromuscular block. These data suggest that there is wide interpatient variability in dosage requirements. In addition, these studies have shown that dosage requirements may decrease or increase with time. Following discontinuation of infusion of atracurium besylate in these ICU studies, spontaneous recovery of four twitches in a train-of-four occurred in an average of approximately 30 minutes (range: 15 to 75 minutes) and spontaneous recovery to a train-of-four ratio >75% (the ratio of height of the fourth to the first twitch in a train-of-four) occurred in an average of approximately 60 minutes (range: 32 to 108 minutes).

Little information is available on the plasma levels and clinical consequences of atracurium metabolites that may accumulate during days to weeks of atracurium administration in ICU patients. Laudanosine, a major biologically active metabolite of atracurium without neuromuscular blocking activity, produces transient hypotension and, in higher doses, cerebral excitatory effects (generalized muscle twitching and seizures) when administered to several species of animals. There have been rare spontaneous reports of seizures in ICU patients who have received atracurium or other agents. These patients usually had predisposing causes (such as head trauma, cerebral edema, hypoxic encephalopathy, viral encephalitis, uremia). There are insufficient data to determine whether or not laudanosine contributes to seizures in ICU patients.

WHENEVER THE USE OF ATRACURIUM OR ANY NEUROMUSCULAR BLOCKING AGENT IS CONTEMPLATED IN THE ICU, IT IS RECOMMENDED THAT NEUROMUSCULAR TRANSMISSION BE MONITORED CONTINUOUSLY DURING ADMINISTRATION WITH THE HELP OF A NERVE STIMULATOR. ADDITIONAL DOSES OF ATRACURIUM OR ANY OTHER NEUROMUSCULAR BLOCKING AGENT SHOULD NOT BE GIVEN BEFORE THERE IS A DEFINITE RESPONSE TO T1 OR TO THE FIRST TWITCH. IF NO RESPONSE IS ELICITED, INFUSION ADMINISTRATION SHOULD BE DISCONTINUED UNTIL A RESPONSE RETURNS.

Hemofiltration has a minimal effect on plasma levels of atracurium and its metabolites, including laudanosine. The effects of hemodialysis and hemoperfusion on plasma levels of atracurium and its metabolites are unknown.

Drug Interactions

Drugs which may enhance the neuromuscular blocking action of atracurium include: enflurane; isoflurane; halothane; certain antibiotics, especially the aminoglycosides and polymyxins; lithium; magnesium salts; procainamide; and quinidine.

If other muscle relaxants are used during the same procedure, the possibility of a synergistic or antagonist effect should be considered.

The prior administration of succinylcholine does not enhance the duration, but quickens the onset and may increase the depth, of neuromuscular block induced by atracurium besylate. Atracurium should not be administered until a patient has recovered from succinylcholine-induced neuromuscular block.

Carcinogenesis, Mutagenesis, Impairment of Fertility

Carcinogenesis and fertility studies have not been performed. Atracurium was evaluated in a battery of three short-term mutagenicity tests. It was non-mutagenic in both the Ames Salmonella assay at concentrations up to 1000 mcg/plate, and in a rat bone marrow cytogenicity assay at up to paralyzing doses. A positive response was observed in the mouse lymphoma assay under conditions (80 and 100 mcg/mL, in the absence of metabolic activation) which killed over 80% of the treated cells; there was no mutagenicity at 60 mcg/mL and lower, concentrations which killed up to half of the treated cells. A far weaker response was observed in the presence of metabolic activation at concentrations (1200 mcg/mL and higher) which also killed over 80% of the treated cells.

Mutagenicity testing is intended to simulate chronic (years to lifetime) exposure in an effort to determine potential carcinogenicity. Thus, a single positive mutagenicity response for a drug used infrequently and/or briefly is of questionable clinical relevance.

Pregnancy

Teratogenic Effects: Pregnancy Category C

Atracurium besylate has been shown to be potentially teratogenic in rabbits when given in doses up to approximately one-half the human dose. There are no adequate and well-controlled studies in pregnant women. Atracurium should be used during pregnancy only if the potential benefit justifies the potential risk to the fetus.

Atracurium besylate was administered subcutaneously on days 6 through 18 of gestation to non-ventilated Dutch rabbits. Treatment groups were given either 0.15 mg/kg once daily or 0.10 mg/kg twice daily. Lethal respiratory distress occurred in two 0.15 mg/kg animals and in one 0.10 mg/kg animal, with transient respiratory distress or other evidence of neuromuscular block occurring in 10 of 19 and in 4 of 20 of the 0.15 mg/kg and 0.10 mg/kg animals, respectively. There was an increased incidence of certain spontaneously occurring visceral and skeletal anomalies or variations in one or both treated groups when compared to non-treated controls. The percentage of male fetuses was lower (41% vs. 51%) and the post-implantation losses were increased (15% vs. 8%) in the group given 0.15 mg/kg once daily when compared to the controls; the mean numbers of implants (6.5 vs. 4.4) and normal live fetuses (5.4 vs. 3.8) were greater in this group when compared to the control group.

Labor and Delivery

It is not known whether muscle relaxants administered during vaginal delivery have immediate or delayed adverse effects on the fetus or increase the likelihood that resuscitation of the newborn will be necessary. The possibility that forceps delivery will be necessary may increase.

Atracurium besylate (0.3 mg/kg) has been administered to 26 pregnant women during delivery by cesarean section. No harmful effects were attributable to atracurium in any of the neonates, although small amounts of atracurium were shown to cross the placental barrier. The possibility of respiratory depression in the neonate should always be considered following cesarean section during which a neuromuscular blocking agent has been administered. In patients receiving magnesium sulfate, the reversal of neuromuscular block may be unsatisfactory and the dose of atracurium besylate should be lowered as indicated.

Nursing Mothers

It is not known whether this drug is excreted in human milk. Because many drugs are excreted in human milk, caution should be exercised when atracurium besylate is administered to a nursing woman.

Pediatric Use

Safety and effectiveness in pediatric patients below the age of 1 month have not been established.

Geriatric Use

Since marketing in 1983, uncontrolled clinical experience and limited data from controlled trials have not identified differences in effectiveness, safety, or dosage requirements between healthy elderly and younger patients (see CLINICAL PHARMACOLOGY); however, as with other neuromuscular blocking agents, the use of a peripheral nerve stimulator to monitor neuromuscular function is suggested (see DOSAGE AND ADMINISTRATION).

ADVERSE REACTIONS

Observed in Controlled Clinical Studies

Atracurium was well tolerated and produced few adverse reactions during extensive clinical trials. Most adverse reactions were suggestive of histamine release. In studies including 875 patients, atracurium was discontinued in only one patient (who required treatment for bronchial secretions) and six other patients required treatment for adverse reactions attributable to atracurium (wheezing in one, hypotension in five). Of the five patients who required treatment for hypotension, three had a history of significant cardiovascular disease. The overall incidence rate for clinically important adverse reactions, therefore, was 7/875 or 0.8%.

Table 1 includes all adverse reactions reported attributable to atracurium during clinical trials with 875

patients.

Table 1: Percent of Patients Reporting Adverse Reactions
Adverse Reaction | Initial Atracurium Dose (mg/kg)
 | 0.00-0.30 (n = 485) | 0.31-0.50* (n = 366) | ≥0.60 (n = 24) | Total (n = 875)
Skin Flush | 1.0% | 8.7% | 29.2% | 5.0%
Erythema | 0.6% | 0.5% | 0% | 0.6%
Itching | 0.4% | 0% | 0% | 0.2%
Wheezing/Bronchial Secretions | 0.2% | 0.3% | 0% | 0.2%
Hives | 0.2% | 0% | 0% | 0.1%
* Includes the recommended initial dosage range for most patients.

Most adverse reactions were of little clinical significance unless they were associated with significant hemodynamic changes. Table 2 summarizes the incidences of substantial vital sign changes noted during atracurium clinical trials with 530 patients, without cardiovascular disease, in whom these parameters were assessed.

Table 2: Percent of Patients Showing >30% Vital Sign Changes Following Administration of Atracurium
Vital Sign Change | Initial Atracurium Dose (mg/kg)
 | 0.00-0.30 (n = 365) | 0.31-0.50* (n = 144) | ≥0.60 (n = 21) | Total (n = 530)
Mean Arterial Pressure
Increase | 1.9% | 2.8% | 0% | 2.1%
Decrease | 1.1% | 2.1% | 14.3% | 1.9%
Heart Rate
Increase | 1.6% | 2.8% | 4.8% | 2.1%
Decrease | 0.8% | 0% | 0% | 0.6%
* Includes the recommended initial dosage range for most patients.

Observed in Clinical Practice

Based on initial clinical practice experience in approximately 3 million patients who received atracurium in the U.S. and in the United Kingdom, spontaneously reported adverse reactions were uncommon (approximately 0.01% to 0.02%). The following adverse reactions are among the most frequently reported, but there are insufficient data to support an estimate of their incidence:

General: Allergic reactions (anaphylactic or anaphylactoid responses) which, in rare instances, were severe (e.g., cardiac arrest)

Musculoskeletal: Inadequate block, prolonged block

Cardiovascular: Hypotension, vasodilatation (flushing), tachycardia, bradycardia

Respiratory: Dyspnea, bronchospasm, laryngospasm

Integumentary: Rash, urticaria, reaction at injection site

There have been rare spontaneous reports of seizures in ICU patients following long-term infusion of atracurium to support mechanical ventilation. There are insufficient data to define the contribution, if any, of atracurium and/or its metabolite laudanosine (see PRECAUTIONS, Long-Term Use in Intensive Care Unit (ICU)).

There have been post-marketing reports of severe allergic reactions (anaphylactic and anaphylactoid reactions) associated with use of neuromuscular blocking agents, including atracurium besylate. These reactions, in some cases, have been life-threatening and fatal. Because these reactions were reported voluntarily from a population of uncertain size, it is not possible to reliably estimate their frequency (see WARNINGS and PRECAUTIONS).

To report SUSPECTED ADVERSE REACTIONS, contact Meitheal Pharmaceuticals Inc. at 1-844-824-8426 or FDA at 1-800-FDA-1088 or www.fda.gov/medwatch.

OVERDOSAGE

There has been limited experience with overdosage of atracurium besylate. The possibility of iatrogenic overdosage can be minimized by carefully monitoring muscle twitch response to peripheral nerve stimulation. Excessive doses of atracurium can be expected to produce enhanced pharmacological effects. Overdosage may increase the risk of histamine release and cardiovascular effects, especially hypotension. If cardiovascular support is necessary, this should include proper positioning, fluid administration, and the use of vasopressor agents if necessary. The patient's airway should be assured, with manual or mechanical ventilation maintained as necessary. A longer duration of neuromuscular block may result from overdosage and a peripheral nerve stimulator should be used to monitor recovery. Recovery may be facilitated by administration of an anticholinesterase reversing agent such as neostigmine, edrophonium, or pyridostigmine, in conjunction with an anticholinergic agent such as atropine or glycopyrrolate. The appropriate package inserts should be consulted for prescribing information.

Three pediatric patients (3 weeks, 4 and 5 months of age) unintentionally received doses of 0.8 mg/kg to 1 mg/kg of atracurium besylate. The time to 25% recovery (50 to 55 minutes) following these doses, which were 5 to 6 times the ED95 dose, was moderately longer than the corresponding time observed following doses 2 to 2.5 times the atracurium ED95 dose in infants (22 to 36 minutes). Cardiovascular changes were minimal. Nonetheless the possibility of cardiovascular changes must be considered in the case of overdose.

An adult patient (17 years of age) unintentionally received an initial dose of 1.3 mg/kg of atracurium besylate. The time from injection to 25% recovery (83 minutes) was approximately twice that observed following maximum recommended doses in adults (35 to 45 minutes). The patient experienced moderate hemodynamic changes (13% increase in mean arterial pressure and 27% increase in heart rate) which persisted for 40 minutes and did not require treatment.

The intravenous LD50s determined in non-ventilated male and female albino mice and male Wistar rats were 1.9, 2.01 and 1.31 mg/kg, respectively. Deaths occurred within 2 minutes and were caused by respiratory paralysis. The subcutaneous LD50 determined in non-ventilated male Wistar rats was 282.8 mg/kg. Tremors, ptosis, loss of reflexes and respiratory failure preceded death which occurred 45 to 120 minutes after injection.

DOSAGE AND ADMINISTRATION

To avoid distress to the patient, atracurium should not be administered before unconsciousness has been induced. Atracurium should not be mixed in the same syringe, or administered simultaneously through the same needle, with alkaline solutions (e.g., barbiturate solutions).

Atracurium besylate should be administered intravenously. DO NOT GIVE ATRACURIUM BESYLATE BY INTRAMUSCULAR ADMINISTRATION. Intramuscular administration of atracurium besylate may result in tissue irritation and there are no clinical data to support this route of administration.

As with other neuromuscular blocking agents, the use of a peripheral nerve stimulator will permit the most advantageous use of atracurium besylate, minimizing the possibility of overdosage or underdosage, and assist in the evaluation of recovery.

Bolus Doses for Intubation and Maintenance of Neuromuscular Block

Adults

An atracurium besylate dose of 0.4 to 0.5 mg/kg (1.7 to 2.2 times the ED95), given as an intravenous bolus injection, is the recommended initial dose for most patients. With this dose, good or excellent conditions for nonemergency intubation can be expected in 2 to 2.5 minutes in most patients, with maximum neuromuscular block achieved approximately 3 to 5 minutes after injection. Clinically required neuromuscular block generally lasts 20 to 35 minutes under balanced anesthesia. Under balanced anesthesia, recovery to 25% of control is achieved approximately 35 to 45 minutes after injection, and recovery is usually 95% complete approximately 60 minutes after injection.

Atracurium is potentiated by isoflurane or enflurane anesthesia. The same initial atracurium besylate dose of 0.4 to 0.5 mg/kg may be used for intubation prior to administration of these inhalation agents; however, if atracurium is first administered under steady-state of isoflurane or enflurane, the initial atracurium besylate dose should be reduced by approximately one-third, i.e., to 0.25 to 0.35 mg/kg, to adjust for the potentiating effects of these anesthetic agents. With halothane, which has only a marginal (approximately 20%) potentiating effect on atracurium, smaller dosage reductions may be considered.

Atracurium besylate doses of 0.08 to 0.10 mg/kg are recommended for maintenance of neuromuscular block during prolonged surgical procedures. The first maintenance dose will generally be required 20 to 45 minutes after the initial atracurium besylate injection, but the need for maintenance doses should be determined by clinical criteria. Because atracurium lacks cumulative effects, maintenance doses may be administered at relatively regular intervals for each patient, ranging approximately from 15 to 25 minutes under balanced anesthesia, slightly longer under isoflurane or enflurane. Higher atracurium doses (up to 0.2 mg/kg) permit maintenance dosing at longer intervals.

Pediatric Patients

No atracurium dosage adjustments are required for pediatric patients two years of age or older. An atracurium besylate dose of 0.3 to 0.4 mg/kg is recommended as the initial dose for infants (1 month to 2 years of age) under halothane anesthesia. Maintenance doses may be required with slightly greater frequency in infants and children than in adults.

Special Considerations

An initial atracurium besylate dose of 0.3 to 0.4 mg/kg, given slowly or in divided doses over one minute, is recommended for adults, children, or infants with significant cardiovascular disease and for adults, children, or infants with any history (e.g., severe anaphylactoid reactions or asthma) suggesting a greater risk of histamine release.

Dosage reductions must be considered also in patients with neuromuscular disease, severe electrolyte disorders, or carcinomatosis in which potentiation of neuromuscular block or difficulties with reversal have been demonstrated. There has been no clinical experience with atracurium in these patients, and no specific dosage adjustments can be recommended. No atracurium dosage adjustments are required for patients with renal disease.

An initial atracurium besylate dose of 0.3 to 0.4 mg/kg is recommended for adults following the use of succinylcholine for intubation under balanced anesthesia. Further reductions may be desirable with the use of potent inhalation anesthetics. The patient should be permitted to recover from the effects of succinylcholine prior to atracurium administration. Insufficient data are available for recommendation of a specific initial atracurium dose for administration following the use of succinylcholine in children and infants.

Use by Continuous Infusion

Infusion in the Operating Room (OR)

After administration of a recommended initial bolus dose of atracurium besylate injection (0.3 to 0.5 mg/kg), a diluted solution of atracurium besylate can be administered by continuous infusion to adults and pediatric patients aged 2 or more years for maintenance of neuromuscular block during extended surgical procedures.

Infusion of atracurium should be individualized for each patient. The rate of administration should be adjusted according to the patient's response as determined by peripheral nerve stimulation. Accurate dosing is best achieved using a precision infusion device.

Infusion of atracurium should be initiated only after early evidence of spontaneous recovery from the bolus dose. An initial infusion rate of 9 to 10 mcg/kg/min may be required to rapidly counteract the spontaneous recovery of neuromuscular function. Thereafter, a rate of 5 to 9 mcg/kg/min should be adequate to maintain continuous neuromuscular block in the range of 89% to 99% in most pediatric and adult patients under balanced anesthesia. Occasional patients may require infusion rates as low as 2 mcg/kg/min or as high as 15 mcg/kg/min.

The neuromuscular blocking effect of atracurium administered by infusion is potentiated by enflurane or isoflurane and, to a lesser extent, by halothane. Reduction in the infusion rate of atracurium should, therefore, be considered for patients receiving inhalation anesthesia. The rate of atracurium infusion should be reduced by approximately one-third in the presence of steady-state enflurane or isoflurane anesthesia; smaller reductions should be considered in the presence of halothane.

In patients undergoing cardiopulmonary bypass with induced hypothermia, the rate of infusion of atracurium required to maintain adequate surgical relaxation during hypothermia (25° to 28°C) has been shown to be approximately half the rate required during normothermia.

Spontaneous recovery from neuromuscular block following discontinuation of atracurium infusion may be expected to proceed at a rate comparable to that following administration of a single bolus dose.

Infusion in the Intensive Care Unit (ICU)

The principles for infusion of atracurium in the OR are also applicable to use in the ICU.

An infusion rate of 11 to 13 mcg/kg/min (range: 4.5 to 29.5) should provide adequate neuromuscular block in adult patients in an ICU. Limited information suggests that infusion rates required for pediatric patients in the ICU may be higher than in adult patients. There may be wide interpatient variability in dosage requirements and these requirements may increase or decrease with time (see PRECAUTIONS, Long-Term Use in Intensive Care Unit (ICU)). Following recovery from neuromuscular block, readministration of a bolus dose may be necessary to quickly re-establish neuromuscular block prior to reinstitution of the infusion.

Infusion Rate Tables

The amount of infusion solution required per minute will depend upon the concentration of atracurium in the infusion solution, the desired dose of atracurium, and the patient's weight. The following tables provide guidelines for delivery, in mL/hr (equivalent to microdrops/min when 60 microdrops = 1 mL), of atracurium solutions in concentrations of 0.2 mg/mL (20 mg in 100 mL) or 0.5 mg/mL (50 mg in 100 mL) with an infusion pump or a gravity flow device.

Table 3: Atracurium Besylate Infusion Rates for a Concentration of 0.2 mg/mL
Patient Weight (kg) | Drug Delivery Rate (mcg/kg/min)
Patient Weight (kg) | 5 | 6 | 7 | 8 | 9 | 10 | 11 | 12 | 13
Patient Weight (kg) | Infusion Delivery Rate (mL/hr)
30 | 45 | 54 | 63 | 72 | 81 | 90 | 99 | 108 | 117
35 | 53 | 63 | 74 | 84 | 95 | 105 | 116 | 126 | 137
40 | 60 | 72 | 84 | 96 | 108 | 120 | 132 | 144 | 156
45 | 68 | 81 | 95 | 108 | 122 | 135 | 149 | 162 | 176
50 | 75 | 90 | 105 | 120 | 135 | 150 | 165 | 180 | 195
55 | 83 | 99 | 116 | 132 | 149 | 165 | 182 | 198 | 215
60 | 90 | 108 | 126 | 144 | 162 | 180 | 198 | 216 | 234
65 | 98 | 117 | 137 | 156 | 176 | 195 | 215 | 234 | 254
70 | 105 | 126 | 147 | 168 | 189 | 210 | 231 | 252 | 273
75 | 113 | 135 | 158 | 180 | 203 | 225 | 248 | 270 | 293
80 | 120 | 144 | 168 | 192 | 216 | 240 | 264 | 288 | 312
90 | 135 | 162 | 189 | 216 | 243 | 270 | 297 | 324 | 351
100 | 150 | 180 | 210 | 240 | 270 | 300 | 330 | 360 | 390

Table 4: Atracurium Besylate Infusion Rates for a Concentration of 0.5 mg/mL
Patient Weight (kg) | Drug Delivery Rate (mcg/kg/min)
Patient Weight (kg) | 5 | 6 | 7 | 8 | 9 | 10 | 11 | 12 | 13
Patient Weight (kg) | Infusion Delivery Rate (mL/hr)
30 | 18 | 22 | 25 | 29 | 32 | 36 | 40 | 43 | 47
35 | 21 | 25 | 29 | 34 | 38 | 42 | 46 | 50 | 55
40 | 24 | 29 | 34 | 38 | 43 | 48 | 53 | 58 | 62
45 | 27 | 32 | 38 | 43 | 49 | 54 | 59 | 65 | 70
50 | 30 | 36 | 42 | 48 | 54 | 60 | 66 | 72 | 78
55 | 33 | 40 | 46 | 53 | 59 | 66 | 73 | 79 | 86
60 | 36 | 43 | 50 | 58 | 65 | 72 | 79 | 86 | 94
65 | 39 | 47 | 55 | 62 | 70 | 78 | 86 | 94 | 101
70 | 42 | 50 | 59 | 67 | 76 | 84 | 92 | 101 | 109
75 | 45 | 54 | 63 | 72 | 81 | 90 | 99 | 108 | 117
80 | 48 | 58 | 67 | 77 | 86 | 96 | 106 | 115 | 125
90 | 54 | 65 | 76 | 86 | 97 | 108 | 119 | 130 | 140
100 | 60 | 72 | 84 | 96 | 108 | 120 | 132 | 144 | 156

Compatibility and Admixtures

Atracurium besylate infusion solutions may be prepared by admixing atracurium besylate injection with an appropriate diluent such as 5% Dextrose Injection, 0.9% Sodium Chloride Injection, or 5% Dextrose and 0.9% Sodium Chloride Injection. Infusion solutions should be used within 24 hours of preparation. Unused solutions should be discarded. Solutions containing 0.2 mg/mL or 0.5 mg/mL atracurium besylate in the above diluents may be stored either under refrigeration or at room temperature for 24 hours without significant loss of potency. Care should be taken during admixture to prevent inadvertent contamination. Visually inspect prior to administration.

Spontaneous degradation of atracurium besylate has been demonstrated to occur more rapidly in Lactated Ringer's solution than in 0.9% sodium chloride solution. Therefore, it is recommended that Lactated Ringer's Injection not be used as a diluent in preparing solutions of atracurium besylate injection for infusion.

Parenteral drug products should be inspected visually for particulate matter and discoloration prior to administration, whenever solution and container permit.

Risk of Medication Errors

Accidental administration of neuromuscular blocking agents may be fatal. Store atracurium besylate injection with the cap and ferrule intact and in a manner that minimizes the possibility of selecting the wrong product.

HOW SUPPLIED

Atracurium Besylate Injection, USP is supplied as follows:

NDC | Atracurium Besylate Injection, USP (10 mg per mL) | Package Factor
71288-701-05 | 50 mg per 5 mL Single-Dose Vial | 10 vials per carton
NDC | Atracurium Besylate Injection, USP (10 mg per mL) | Package Factor
71288-702-10 | 100 mg per 10 mL Multi-Dose Vial | 10 vials per carton
 | (contains benzyl alcohol – see WARNINGS)

Storage Conditions

Store between 2° and 8°C (36° and 46°F) to preserve potency.

Upon removal from refrigeration to room temperature storage conditions (25°C/77°F), use Atracurium

Besylate Injection within 14 days even if re-refrigerated.

Protect from light. Retain in carton until time of use.
Do not freeze.

Sterile, Nonpyrogenic.
The container closure is not made with natural rubber latex.

meitheal®
Mfd. for Meitheal Pharmaceuticals
Chicago, IL 60631 (USA)
Made in China
©2018 Meitheal Pharmaceuticals Inc.

Revised: July 2018

Principal Display Panel – Atracurium Besylate Injection, USP 50 mg Vial Label

NDC 71288-701-06

Rx only

Atracurium Besylate Injection, USP

50 mg per 5 mL

(10 mg per mL)

WARNING: Paralyzing Agent

5 mL Single-Dose Vial

For Intravenous Injection

Principal Display Panel – Atracurium Besylate Injection, USP 50 mg Carton

NDC 71288-701-05

10 x 5 mL Single-Dose Vials

Atracurium Besylate Injection, USP

50 mg per 5 mL

(10 mg per mL)

WARNING: Paralyzing Agent

Rx only

For Intravenous Injection

WARNING: Paralyzing Agent. Causes Respiratory Arrest.

Facilities must be immediately available for artificial respiration.

Principal Display Panel - Atracurium Besylate Injection, USP 100 mg Vial Label

NDC 71288-702-11

Rx only

Atracurium Besylate Injection, USP

100 mg per 10 mL

(10 mg per mL)

WARNING: Paralyzing Agent

10 mL Multi-Dose Vial

For Intravenous Injection

Principal Display Panel – Atracurium Besylate Injection, USP 100 mg Carton

NDC 71288-702-10

10 x 10 mL Multi-Dose Vials

Atracurium Besylate Injection, USP

100 mg per 10 mL

(10 mg per mL)

WARNING: Paralyzing Agent

Rx only

For Intravenous Injection

WARNING: Paralyzing Agent. Causes Respiratory Arrest.

Facilities must be immediately available for artificial respiration.